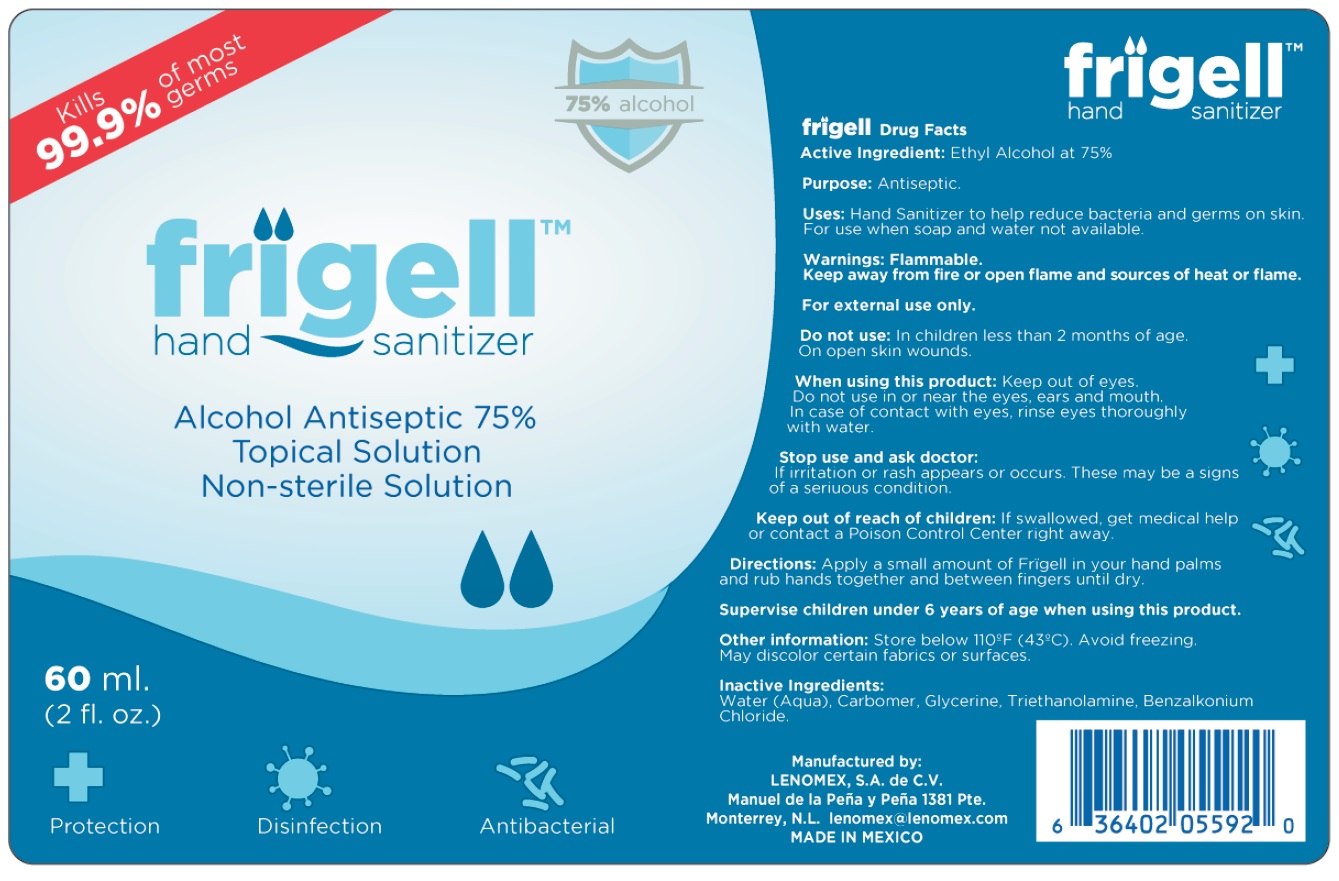 DRUG LABEL: Frigell Hand Sanitizer
NDC: 79251-000 | Form: GEL
Manufacturer: Lenomex, S.A. de C.V.
Category: otc | Type: HUMAN OTC DRUG LABEL
Date: 20200724

ACTIVE INGREDIENTS: ALCOHOL 0.75 mL/1 mL
INACTIVE INGREDIENTS: WATER; CARBOMER HOMOPOLYMER, UNSPECIFIED TYPE; GLYCERIN; TROLAMINE; BENZALKONIUM CHLORIDE

Frigell Hand Sanitizer

Active Ingredient:

Ethyl Alcohol at 75%

Purpose:

Antiseptic

Uses:

Hand Sanitizer to help reduce bacteria and germs on skin. For use when soap and water not available.

Warnings:

Flammable. Keep away from fire or open flame and sources of heat or flame.

For external use only.

Do not use:

In children less than 2 months of age. On open skin wounds.

When using this product:

Keep out of eyes. Do not use in or near the eyes, ears and mouth. In case of contact with eyes, rinse eyes thoroughly

Stop use and ask doctor:

If irritation or rash appears or occurs. These may be a signs of a serious condition.

Keep out of reach of children:

If swallowed, get medical help or contact a Poison Control Center right away.

Directions:

Apply a small amount of Frigell in your hand palms and rub hands together and between fingers until dry.

Supervise children under 6 years of age when using this product.

Other Information:

Store below 110°F (43°C). Avoid freezing. May discolor certain fabrics or surfaces.

Inactive Ingredients:

Water (Aqua), Carbomer, Glycerine, Triethanolamine, Benzalkonium Chloride.